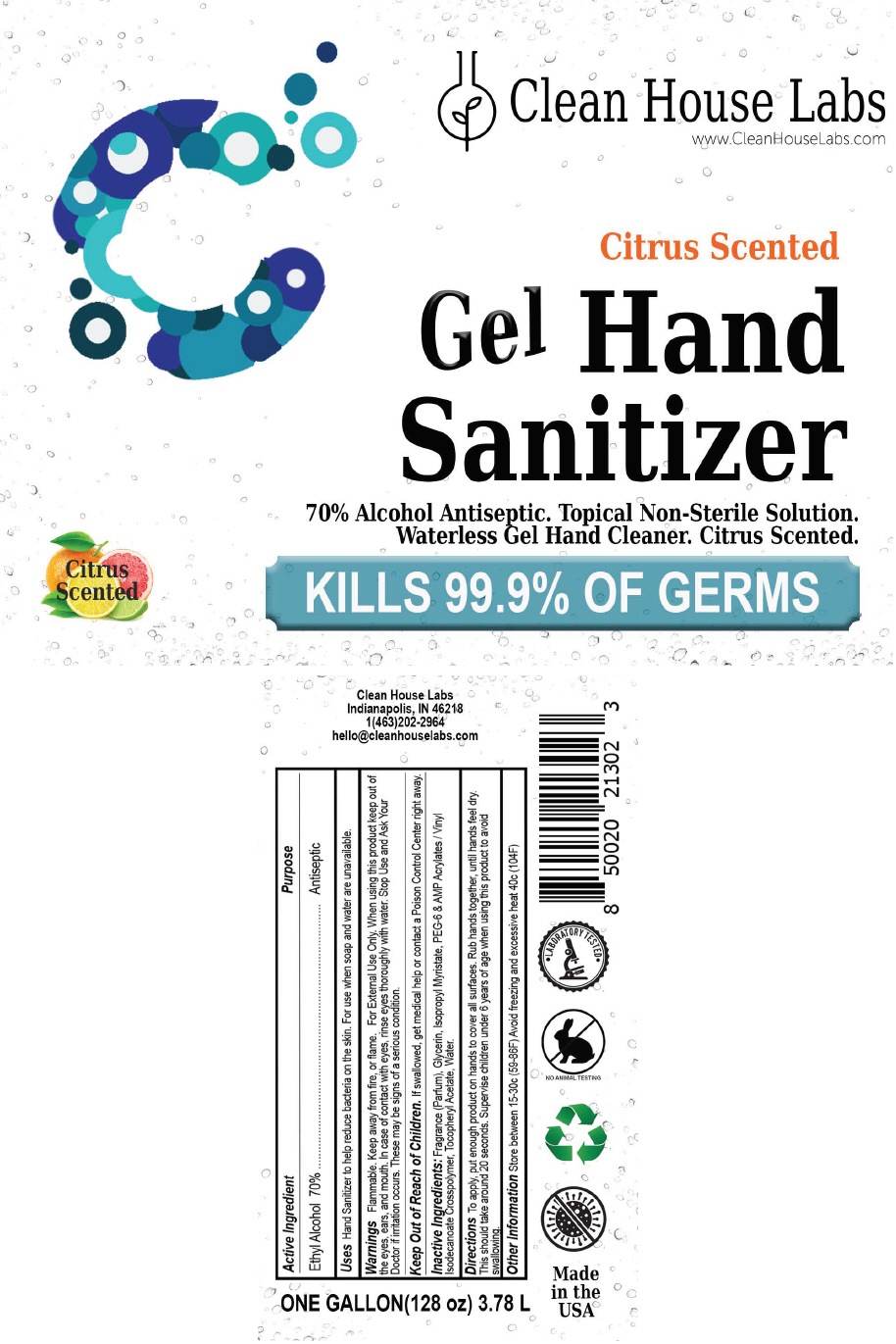 DRUG LABEL: Clean House Labs Hand Sanitizer
NDC: 79964-001 | Form: GEL
Manufacturer: Clean House Labs
Category: otc | Type: HUMAN OTC DRUG LABEL
Date: 20200903

ACTIVE INGREDIENTS: Alcohol 70 mL/100 mL
INACTIVE INGREDIENTS: Water; Glycerin; Aloe; .Alpha.-Tocopherol Acetate; Trolamine; Carbomer Homopolymer, Unspecified Type; Propylene Glycol

Clean House Labs Gel Hand Sanitizer

Active Ingredient

Ethyl Alcohol 70%

Purpose

Antiseptic

Uses

Hand Sanitizer to help reduce bacteria on the skin. For use when soap and water are unavailable.

Warnings

Flammable. Keep away from fire, or flame. For External Use Only. When using this product keep out of the eyes, ears, and mouth. In case of contact with eyes, rinse eyes thoroughly with water. Stop Use and Ask Your Doctor if irritation occurs. These may be signs of a serious condition.

Keep Out of Reach of Children. If swallowed, get medical help or contact a Poison Control Center right away.

Inactive Ingredients

Fragrance (Parfum), Glycerin, Isopropyl Myristate, PEG-6 & AMP Acrylates / Vinyl Isodecanoate Crosspolymer, Tocopheryl Acetate, Water.

Directions

To apply, put enough product on hands to cover all surfaces. Rub hands together, until hands feel dry. This should take around 20 seconds. Supervise children under 6 years of age when using this product to avoid swallowing.

Other Information

Store between 15-30c (59-86F) Avoid freezing and excessive heat 40c (104F)

PRINCIPAL DISPLAY PANEL - 3.78 L Bottle Label

Clean House Labs
www.CleanHouseLabs.com

Citrus Scented
Gel Hand
Sanitizer

70% Alcohol Antiseptic. Topical Non-Sterile Solution.
Waterless Gel Hand Cleaner. Citrus Scented.

Citrus
Scented

KILLS 99.9% OF GERMS